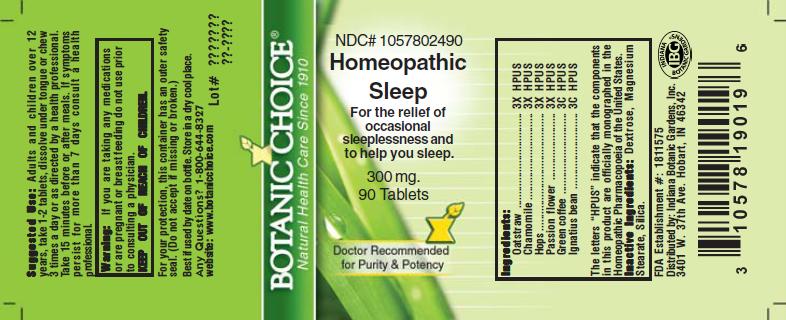 DRUG LABEL: Homeopathic Sleep Formula
NDC: 10578-024 | Form: TABLET
Manufacturer: Indiana Botanic Gardens
Category: homeopathic | Type: HUMAN OTC DRUG LABEL
Date: 20110325

ACTIVE INGREDIENTS: AVENA SATIVA FLOWERING TOP 3 [hp_X]/1 1; MATRICARIA RECUTITA 3 [hp_X]/1 1; HOPS 3 [hp_X]/1 1; PASSIFLORA INCARNATA TOP 3 [hp_X]/1 1; ARABICA COFFEE BEAN 3 [hp_C]/1 1; STRYCHNOS IGNATII SEED 3 [hp_C]/1 1
INACTIVE INGREDIENTS: DEXTROSE; MAGNESIUM STEARATE ; SILICON DIOXIDE 

Homeopathic Sleep Formula

ACTIVE INGREDIENT

I n g r e d i e n t s :

Oatstraw.............................. 3X HPUS
Chamomile.................... 3X HPUS
Hops......................... 3X HPUS
Passion flower.................... 3X HPUS
Green coffee.............................. 3C HPUS
Ignatius bean............................. 3C HPUS

The letters “HPUS” indicate that the components in
this product are officially monographed in the
Homeopathic Pharmacopoeia of the United States.

PURPOSE

For the relief of occasional sleeplessness and to help you sleep

KEEP OUT OF
REACH OF CHILDREN.

INDICATIONS AND USAGE

For the relief of occasional sleeplessness and to help you sleep

WARNINGS

Warning: If you are taking any medications or
are pregnant or breast feeding do not use prior to
consulting a physician.

DOSAGE AND ADMINISTRATION

Suggested Use: Adults and children over 12
years, take 1-2 tablets, dissolve under tongue or
chew 3 times a day or as directed by a health care
professional. Take 15 minutes before or after meals.
If symptoms persist for more than 7 days consult a
health professional.

Inactive Ingredients: Dextrose, Magnesium
Stearate, Silica.

PACKAGE LABEL

NDC# 1057802490

Homeopathic Sleep Formula

For the relief of occasional sleeplessness and to help you sleep

300 mg.
90 Tablets

USER SAFETY WARNINGS

For your protection, this container has an outer
safety seal. (Do not accept if missing or broken.)
Best if used by date on bottle. Store in a dry cool place.
Any Questions? 1-800-644-8327
website: www.botanicchoice.com

FDA Establishment #: 1811575

Distributed by: Indiana Botanic Gardens, Inc.
3401 W. 37th Ave. Hobart, IN 46342